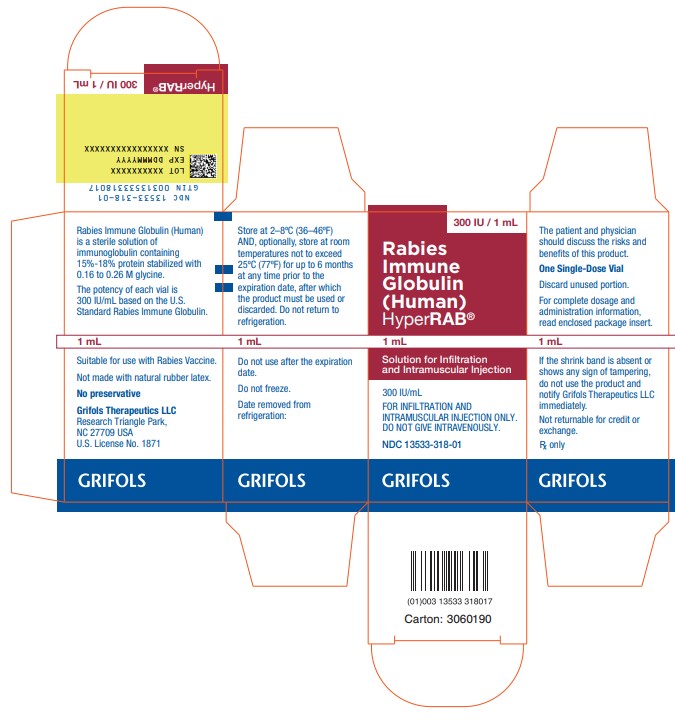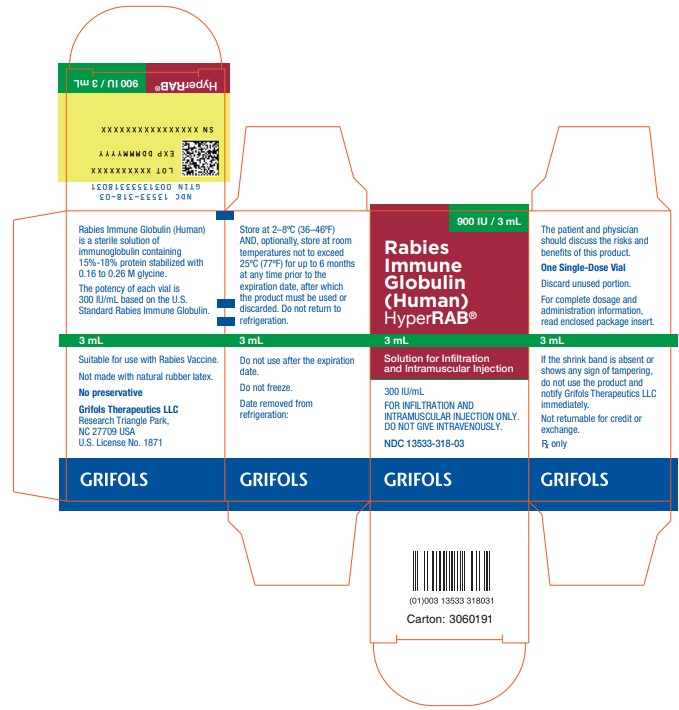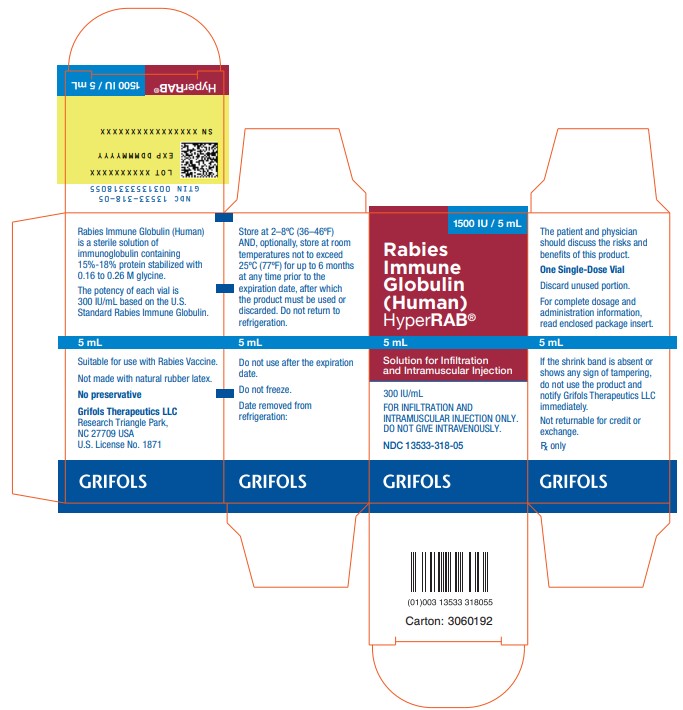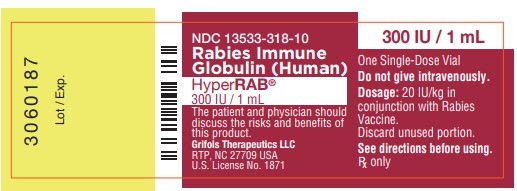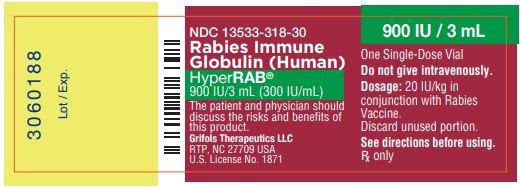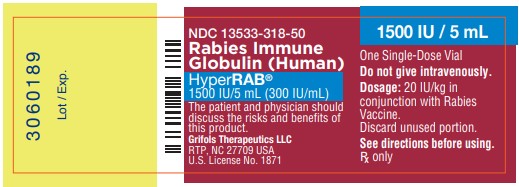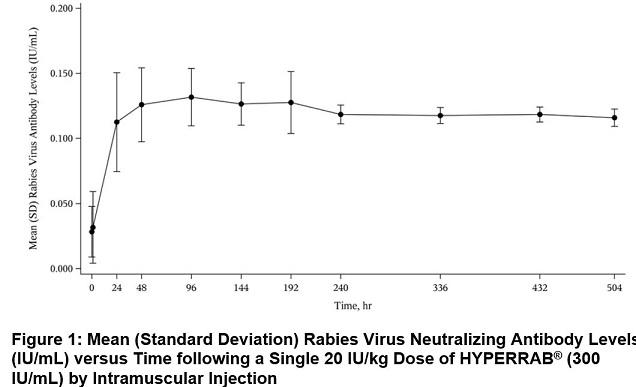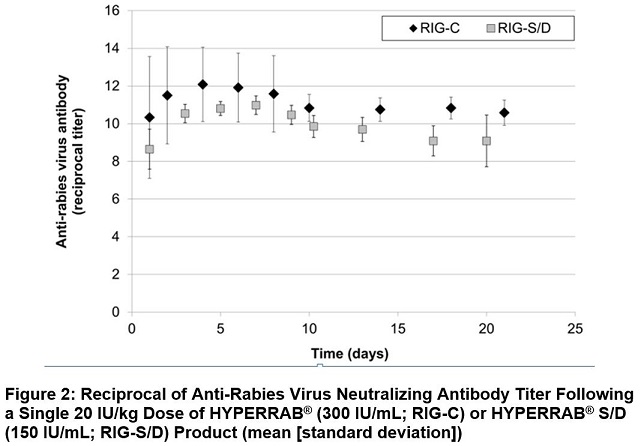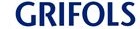 DRUG LABEL: HyperRAB
NDC: 13533-318 | Form: INJECTION, SOLUTION
Manufacturer: GRIFOLS USA, LLC
Category: other | Type: PLASMA DERIVATIVE
Date: 20240920

ACTIVE INGREDIENTS: Human Rabies Virus Immune Globulin 300 [iU]/1 mL
INACTIVE INGREDIENTS: Glycine; Water

HIGHLIGHTS OF PRESCRIBING INFORMATION

These highlights do not include all the information needed to use HYPERRAB safely and effectively. See full prescribing information for HYPERRAB.
HYPERRAB [rabies immune globulin (human)] solution for infiltration and intramuscular injection
Initial U.S. Approval: 1974

1 INDICATIONS AND USAGE

HYPERRAB® is a human rabies immune globulin indicated for postexposure prophylaxis, along with rabies vaccine, for all persons suspected of exposure to rabies. (1)

Limitations of Use

Persons previously immunized with rabies vaccine that have a confirmed adequate rabies antibody titer should receive only vaccine.

For unvaccinated persons, the combination of HYPERRAB and vaccine is recommended for both bite and nonbite exposures regardless of the time interval between exposure and initiation of postexposure prophylaxis.

Beyond 7 days (after the first vaccine dose), HYPERRAB is not indicated since an antibody response to vaccine is presumed to have occurred.

2 DOSAGE AND ADMINISTRATION

For infiltration and intramuscular use only.

Administer HYPERRAB within 7 days after the first dose of rabies vaccine.

Postexposure prophylaxis, along with rabies vaccine, after suspected exposure to rabies (2.1) | HYPERRAB 20 IU/kg body weight OR 0.0665 mL/kg body weight Single-dose | - Administer as soon as possible after exposure, preferably at the time of the first rabies vaccine dose. - Infiltrate the full dose of HYPERRAB thoroughly in the area around and into the wound(s), if anatomically feasible. - Inject the remainder, if any, intramuscularly.

3 DOSAGE FORMS AND STRENGTHS

- 300 IU/mL solution for injection supplied in 1 mL, 3mL and 5 mL single-dose vials. (3)

4 CONTRAINDICATIONS

- None. (4)

5 WARNINGS AND PRECAUTIONS

- Severe hypersensitivity reactions, including anaphylaxis, may occur with HYPERRAB. Have epinephrine available immediately to treat any acute severe hypersensitivity reactions. (5.1)
- HYPERRAB is made from human blood, it may carry a risk of transmitting infectious agents, e.g., viruses, the variant Creutzfeldt-Jakob disease (vCJD) agent, and, theoretically, the Creutzfeldt-Jakob disease (CJD) agent. (5.2)

6 ADVERSE REACTIONS

The most common adverse reactions in >5% of subjects in clinical trials were injection site pain, headache, injection site nodule, abdominal pain, diarrhea, flatulence, nasal congestion, and oropharyngeal pain. (6.1)

To report SUSPECTED ADVERSE REACTIONS, contact Grifols Therapeutics LLC at 1-800-520-2807 or FDA at 1-800-FDA-1088 or www.fda.gov/medwatch.

7 DRUG INTERACTIONS

- Repeated dosing after administration of rabies vaccine may suppress the immune response to the vaccine. (7)
- Defer live vaccine (measles, mumps, rubella) administration for 4 months. (7)

FULL PRESCRIBING INFORMATION

1 INDICATIONS AND USAGE

HYPERRAB is a human rabies immune globulin indicated for postexposure prophylaxis, along with rabies vaccine, for all persons suspected of exposure to rabies.

Limitations of Use

Persons who have been previously immunized with rabies vaccine and have a confirmed adequate rabies antibody titer should receive only vaccine.(1-3)

For unvaccinated persons, the combination of HYPERRAB and vaccine is recommended for both bite and nonbite exposures regardless of the time interval between exposure and initiation of postexposure prophylaxis.(1-3)

Beyond 7 days (after the first vaccine dose), HYPERRAB is not indicated since an antibody response to vaccine is presumed to have occurred.

2 DOSAGE AND ADMINISTRATION

For infiltration and intramuscular use only.

The strength of HYPERRAB is 300 IU/mL.

2.1 Dose

Use HYPERRAB in combination with rabies vaccine series to be effective. Do not use HYPERRAB alone for prevention.

Administer HYPERRAB within 7 days after the first dose of rabies vaccine.

Rabies Postexposure Prophylaxis Schedule [Adapted from reference ‎1.]
Vaccination Status | Treatment | Regimen [These regimens are applicable for all age groups, including children.]
Not previously vaccinated | Wound cleansing | • Cleanse all wounds immediately and thoroughly with soap and water. • Irrigate the wounds with a virucidal agent such as a povidone-iodine solution, if available.
Not previously vaccinated | HYPERRAB 20 IU/kg body weight OR 0.0665 mL/kg body weight Single-dose | • Administer HYPERRAB as soon as possible after exposure, preferably at the time of the first vaccine dose. • Infiltrate the full dose of HYPERRAB thoroughly in the area around and into the wound(s), if anatomically feasible. [see Dosage and Administration (‎2.3)] • Inject the remainder, if any, intramuscularly at an anatomical site distant from the site of vaccine administration. [see Dosage and Administration (‎2.3)] • Do not exceed the recommended dose of HYPERRAB, otherwise the active production of rabies antibody may be partially suppressed. [see Drug Interactions (7)] • Use separate syringes, needles, and anatomical injection sites for HYPERRAB and for rabies vaccine.
Not previously vaccinated | Rabies Vaccine | • Administer rabies vaccine on day 0 [Day 0 is the day the first dose of vaccine is administered. Refer to vaccine manufacturer’s instructions or to the recommendations of the Advisory Committee on Immunization Practices (ACIP)(1-3) for appropriate rabies vaccine formulations, schedules and dosages.] • Complete a rabies vaccination series for previously unvaccinated persons.
Previously vaccinated [Any person with a history of rabies vaccination and a documented history of antibody response to the prior vaccination.] | Wound cleansing | • Cleanse all wounds immediately and thoroughly with soap and water. • Irrigate the wounds with a virucidal agent such as a povidone-iodine solution, if available.
Previously vaccinated [Any person with a history of rabies vaccination and a documented history of antibody response to the prior vaccination.] | HYPERRAB | • Do not administer HYPERRAB. [see Indications and Usage (‎1)]
Previously vaccinated [Any person with a history of rabies vaccination and a documented history of antibody response to the prior vaccination.] | Rabies Vaccine | • Administer rabies vaccine on day 0‡. • Complete a rabies vaccination series for previously vaccinated persons.

2.2 Preparation

- Calculate the volume of HYPERRAB for the recommended dose of 20 IU/kg.
- Ensure the correct strength is used for the calculation. HYPERRAB is formulated with a strength of 300 IU/mL. The predecessor product, HYPERRAB® S/D [rabies immune globulin (human)] was formulated at 150 IU/mL. The volume required of HYPERRAB (300 IU/mL) to achieve the recommended dose of 20 IU/kg is approximately one half of that required for the previous HYPERRAB S/D (150 IU/mL).
- Visually inspect parenteral drug products for particulate matter and discoloration prior to administration, whenever solution and container permit. HYPERRABis a clear or slightly opalescent, and colorless or pale yellow sterile solution.
- Do not use HYPERRAB if the product shows any sign of tampering. Notify Grifols Therapeutics LLC immediately [1-800-520-2807].
- Do not freeze. Do not use any solution that has been frozen.
- Discard unused portion.

2.3 Administration

- Administer HYPERRAB at the time of the first vaccine dose (day 0), but no later than day 7.(1-3)
- Infiltrate the full dose of HYPERRAB in the area around the wound, if anatomically feasible. Dilute HYPERRAB with an equal volume of dextrose, 5% (D5W), if additional volume is needed to infiltrate the entire wound. Do not dilute with normal saline.
- Inject the remainder, if any, of the HYPERRAB dose intramuscularly into the deltoid muscle of the upper arm or into the lateral thigh muscle, and distant from the site of vaccine administration.
- Do not administer HYPERRAB in the same syringe or needle or in the same anatomic site as vaccine.

3 DOSAGE FORMS AND STRENGTHS

HYPERRAB is a sterile, 300 IU/mL solution for injection supplied in 1 mL, 3 mL and 5 mL single-dose vials. The 1 mL vial is sufficient for a child weighing 15 kg. The 3 mL vial is sufficient for a person weighing 45 kg. The 5 mL vial is sufficient for an adult weighing 75 kg.

HYPERRAB is standardized against the U.S. Standard Rabies Immune Globulin to contain a potency of ≥300 IU/mL. The U.S. unit of potency is equivalent to the international unit (IU) for rabies antibody.

4 CONTRAINDICATIONS

None.

5 WARNINGS AND PRECAUTIONS

5.1 Hypersensitivity Reactions

Severe hypersensitivity reactions may occur with HYPERRAB. Patients with a history of prior systemic allergic reactions to human immunoglobulin preparations are at a greater risk of developing severe hypersensitivity and anaphylactic reactions. Have epinephrine available for treatment of acute allergic symptoms, should they occur.

Patients with isolated immunoglobulin A (IgA) deficiency may develop severe hypersensitivity reactions to HYPERRAB, or subsequently, to the administration of blood products that contain IgA.(4)

5.2 Transmissible Infectious Agents

HYPERRAB is made from human blood and may carry a risk of transmitting infectious agents, e.g., viruses, the variant Creutzfeldt-Jakob disease (vCJD) agent, and, theoretically, the Creutzfeldt-Jakob disease (CJD) agent. HYPERRAB is purified from human plasma obtained from healthy donors. When medicinal biological products are administered, infectious diseases due to transmission of pathogens cannot be totally excluded. However, in the case of products prepared from human plasma, the risk of transmission of pathogens is reduced by: (1) epidemiological controls on the donor population and selection of individual donors by a medical interview and screening of individual donations and plasma pools for viral infection markers; (2) testing of plasma for hepatitis C virus (HCV), human immunodeficiency virus (HIV), hepatitis B virus (HBV), HAV and human parvovirus (B19V) genomic material; and (3) manufacturing procedures with demonstrated capacity to inactivate/remove pathogens.

ALL infections thought by a physician possibly to have been transmitted by this product should be reported by the physician or other healthcare provider to Grifols Therapeutics LLC [1-800-520-2807].

6 ADVERSE REACTIONS

The most common adverse reactions in >5% of subjects during clinical trials were injection site pain, headache, injection site nodule, abdominal pain, diarrhea, flatulence, nasal congestion, and oropharyngeal pain.

6.1 Clinical Trials Experience

Because clinical trials are conducted under widely varying conditions, adverse reaction rates observed in the clinical trials of a drug cannot be directly compared to rates in the clinical trials of another drug and may not reflect the rates observed in practice.

The new formulation for HYPERRAB is manufactured using caprylate/chromatography purification and has a rabies antibody concentration of 300 IU/mL. The previous formulation, HYPERRAB S/D, was manufactured using a solvent detergent process andhad a rabies antibody concentration of 150 IU/mL. These products were evaluated in 2 clinical trials in a total of 20 healthy subjects using a 20 IU/kg single-dose. The initial study evaluated the original 150 IU/mL HYPERRAB S/D in 8 subjects and the second study evaluated HYPERRAB in 12 subjects. The original study of HYPERRAB S/D reported headache (1/8; 13%).

In the study with HYPERRAB at 300 IU/mL, 5 subjects (5/12; 42%) experienced at least 1 adverse reaction. These were: injection site pain (4/12; 33%), injection site nodule (1/12; 8%), abdominal pain (1/12; 8%), diarrhea (1/12; 8%), flatulence (1/12; 8%), headache (1/12; 8%), nasal congestion (1/12; 8%), and oropharyngeal pain (1/12; 8%).

6.2 Postmarketing Experience

There are no data on the postmarketing use of HYPERRAB (300 IU/mL). The following adverse reactions have been identified during post approval use of the predecessor formulation, HYPERRAB S/D. Because these reactions are reported voluntarily from a population of uncertain size, it is not always possible to reliably estimate their frequency or establish a causal relationship to drug exposure.

Among patients treated with HYPERRAB S/D, cases of allergic/hypersensitivity reactions including anaphylaxis have been reported. Soreness at the site of injection (injection site pain) may be observed following intramuscular injection of immune globulins. Sensitization to repeated injections has occurred occasionally in immunoglobulin-deficient patients.

The following have been identified as the most frequently reported post-marketing adverse reactions:

Immune system disorder | Anaphylactic reaction [These reactions have been manifested by dizziness, paresthesia, rash, flushing, dyspnea, tachypnea, oropharyngeal pain, hyperhidrosis, and erythema.] , hypersensitivity
Nervous system disorders | Hypoesthesia
Gastrointestinal disorders | Nausea
Musculoskeletal and connective tissue disorders | Arthralgia, myalgia, pain in extremity

7 DRUG INTERACTIONS

- Do not administer repeated doses of HYPERRAB once vaccine treatment has been initiated as this could prevent the full expression of active immunity expected from the rabies vaccine.(1)
- Other antibodies in the HYPERRAB preparation may interfere with the response to live vaccines such as measles, mumps, polio or rubella. Defer immunization with live vaccines for 4 months after HYPERRAB administration.(5)

8 USE IN SPECIFIC POPULATIONS

8.1 Pregnancy

Risk Summary

There are no data with HYPERRAB use in pregnant women to inform a drug-associated risk. Animal reproduction studies have not been conducted with HYPERRAB. It is not known whether HYPERRAB can cause fetal harm when administered to a pregnant woman or can affect reproduction capacity. HYPERRAB should be given to a pregnant woman only if clearly needed. In the U.S. general population, the estimated backgrounds risk of major birth defect and miscarriage in clinically recognized pregnancies is 2-4% and 15-20%, respectively.

8.2 Lactation

Risk Summary

There is no information regarding the presence of HYPERRAB in human milk, the effect on the breastfed infant, or the effects on milk production. The developmental and health benefits of breastfeeding should be considered along with the mother’s clinical need for HYPERRAB and any potential adverse effects on the breastfed infant from HYPERRAB.

8.4 Pediatric Use

Safety and effectiveness in the pediatric population have not been established.

8.5 Geriatric Use

Safety and effectiveness in geriatric population have not been established.

10 OVERDOSAGE

Because rabies immune globulin (human) may partially suppress active production of antibody in response to the rabies vaccine, do not give more than the recommended dose of rabies immune globulin (human).(1)

11 DESCRIPTION

HYPERRAB is a clear or slightly opalescent, and colorless or pale yellow sterile solution of human antirabies immune globulin for infiltration and intramuscular administration. HYPERRAB is provided in a single-dose vial and contains no preservative. HYPERRAB is prepared from pools of human plasma collected from healthy donors (hyperimmunized with rabies vaccine) by a combination of cold ethanol fractionation, caprylate precipitation and filtration, caprylate incubation, anion-exchange chromatography, nanofiltration and low pH incubation. HYPERRAB consists of 15 to 18% protein at pH 4.1 to 4.8 in 0.16 to 0.26 M glycine. The product is standardized against the U.S. Standard Rabies Immune Globulin to contain a potency value of not less than 300 IU/mL. The U.S. unit of potency is equivalent to the international unit (IU) for rabies antibody.

When medicinal biological products are administered, infectious diseases due to transmission of pathogens cannot be totally excluded. However, in the case of products prepared from human plasma, the risk of transmission of pathogens is reduced by epidemiological surveillance of the donor population and selection of individual donors by medical interview; testing of individual donations and plasma pools; and the presence in the manufacturing processes of steps with demonstrated capacity to inactivate/remove pathogens.

In the manufacturing process of HYPERRAB, there are several steps with the capacity for virus inactivation or removal.(6) The main steps of the manufacturing process that contribute to the virus clearance capacity are as follows:

- Caprylate precipitation/depth filtration
- Caprylate incubation
- Depth filtration
- Column chromatography
- Nanofiltration
- Low pH final container incubation

To provide additional assurance of the pathogen safety of the final product, the capacity of the HYPERRAB manufacturing process to remove and/or inactivate viruses has been demonstrated by laboratory spiking studies on a scaled down process model using a wide range of viruses with diverse physicochemical properties.

The combination of all of the above mentioned measures provides the final product with a high margin of safety from the potential risk of transmission of infectious viruses.

The caprylate/chromatography manufacturing process was also investigated for its capacity to decrease the infectivity of an experimental agent of transmissible spongiform encephalopathy (TSE), considered as a model for the variant Creutzfeldt-Jakob disease (vCJD), and Creutzfeldt-Jakob disease (CJD) agents.(6) These studies provide reasonable assurance that low levels of vCJD/CJD agent infectivity, if present in the starting material, would be removed by the caprylate/chromatography manufacturing process.

12 CLINICAL PHARMACOLOGY

12.1 Mechanism of Action

HYPERRAB provides immediate, passive, rabies virus neutralizing antibody coverage until the previously unvaccinated patient responds to rabies vaccine by actively producing antibodies.(1)

12.2 Pharmacodynamics

The usefulness of prophylactic rabies antibody in preventing rabies in humans when administered immediately after exposure was dramatically demonstrated in a group of persons bitten by a rabid wolf in Iran.(7,8) Similarly, beneficial results were later reported from the U.S.S.R.(9) Studies coordinated by WHO (World Health Organization) helped determine the optimal conditions under which antirabies serum of equine origin and rabies vaccine can be used in man.(10-13) These studies showed that antirabies serum can interfere to a variable extent with the active immunity induced by the vaccine, but could be minimized by booster doses of vaccine after the end of the usual dosage series.

Preparation of rabies immune globulin of human origin with adequate potency was reported by Cabasso et al.(14) In carefully controlled clinical studies, this globulin was used in conjunction with rabies vaccine of duck-embryo origin (DEV).(14,15) These studies determined that a human globulin dose of 20 IU/kg of rabies antibody, given simultaneously with the first DEV dose, resulted in amply detectable levels of passive rabies antibody 24 hours after injection in all recipients. The injections produced minimal, if any, interference with the subject's endogenous antibody response to DEV.

Subsequently, human diploid cell rabies vaccines (HDCV) prepared from tissue culture fluids containing rabies virus have received substantial clinical evaluation in Europe and the United States.14-22 In a study in adult volunteers, the administration of rabies immune globulin (human) did not interfere with antibody formation induced by HDCV when given in a dose of 20 IU per kilogram body weight simultaneously with the first dose of vaccine.‎(21)

12.3 Pharmacokinetics

In a clinical study of 12 healthy human subjects receiving a 20 IU/kg intramuscular dose of HYPERRAB detectable passive rabies neutralizing antibody was present by 24 hours and persisted through the 21 day follow-up evaluation period. Figure 1 shows the mean levels of rabies virus antibodies in IU/mL across the 21 day evaluation period and indicates that the titer remains stable during this period. This level of passive rabies neutralizing antibody is similar to that reported in the literature for administration of human rabies immune globulin, and is clinically important because it provides interim protection until the host immune response to rabies vaccine produces definitive protective titers of neutralizing rabies antibody (therefore the rabies vaccine series is also essential).(23-24)

The previous formulation, HYPERRAB S/D, was studied in 8 healthy subjects over 21 days. As with the new formulation, rabies neutralizing antibody was present by 24 hours and persisted through the 21 day follow up period (Figure 2).

14 CLINICAL STUDIES

HYPERRAB was administered to a total of 20 healthy adult subjects in two clinical trials. [see Clinical Pharmacology (12.3)] A single intramuscular dose of 20 IU/kg HYPERRAB (12 subjects) or HYPERRAB S/D (8 subjects) was administered and rabies neutralizing antibody titers were monitored in serum for 21 days. Administration of both HYPERRAB formulations resulted in detectable titers of neutralizing antibodies to the rabies virus that persisted throughout the 21 day study period (Figure 2).

15 REFERENCES

1. Centers for Disease Control and Prevention. Human rabies prevention — United States, 2008: Recommendations of the Advisory Committee on Immunization Practices. MMWR. 2008;57(RR03):1-26, 28.
2. World Health Organization. WHO Expert Consultation on Rabies: Second report. 2013. WHO technical report series, No. 982.
3. Centers for Disease Control and Prevention. Use of a reduced (4-dose) vaccine schedule for postexposure prophylaxis to prevent human rabies. Recommendations of the Advisory Committee on Immunization Practices. MMWR. 2010;59(RR02):1-9. Erratum in: MMWR 2010;59(16):493.
4. Fudenberg HH. Sensitization to immunoglobulins and hazards of gamma globulin therapy. In: Merler E (editor). Immunoglobulins: biologic aspects and clinical uses. Washington, DC: National Academy of Science; 1970, p. 211-20.
5. Centers for Disease Control and Prevention. General recommendations on immunization: Recommendations of the Advisory Committee on Immunization Practices (ACIP). MMWR. 2011;60(RR02):1-61. Erratum in: MMWR. 2011;60(29):993.
6. Barnette D, Roth NJ, Hotta J, et al. Pathogen safety profile of a 10% IgG preparation manufactured using a depth filtration-modified process. Biologicals. 2012;40:247-53.
7. Baltazard M, Bahmanyar M, Ghodssi M, et al. Essai pratique du sérum antirabique chez les mordus par loups enragés. [Practical test of anti-rabies serum in bites by rabid wolves]. Bull WHO. 1955;13:747-72.
8. Habel K, Koprowski H. Laboratory data supporting the clinical trial of antirabies serum in persons bitten by a rabid wolf. Bull WHO. 1955;13:773-9.
9. Selimov M, Boltucij L, Semenova E, et al. [The use of antirabies gamma globulin in subjects severely bitten by rabid wolves or other animals.] J Hyg Epidemiol Microbiol Immunol (Praha). 1959;3:168-80.
10. Atanasiu P, Bahmanyar M, Baltazard M, et al. Rabies neutralizing antibody response to different schedules of serum and vaccine inoculations in non-exposed persons. Bull WHO. 1956;14:593-611.
11. Atanasiu P, Bahmanyar M, Baltazard M, et al. Rabies neutralizing antibody response to different schedules of serum and vaccine inoculations in non-exposed persons: Part II. Bull WHO. 1957;17:911-32.
12. Atanasiu P, Cannon DA, Dean DJ, et al. Rabies neutralizing antibody response to different schedules of serum and vaccine inoculations in non-exposed persons: Part 3. Bull WHO. 1961;25:103-14.
13. Atanasiu P, Dean DJ, Habel K, et al. Rabies neutralizing antibody response to different schedules of serum and vaccine inoculations in non-exposed persons: Part 4. Bull WHO. 1967;36:361-5.
14. Cabasso VJ, Loofbourow JC, Roby RE, et al. Rabies immune globulin of human origin: preparation and dosage determination in non-exposed volunteer subjects. Bull WHO. 1971;45:303-15.
15. Loofbourow JC, Cabasso VJ, Roby RE, et al. Rabies immune globulin (human): clinical trials and dose determination. JAMA. 1971;217(13):1825-31.
16. Plotkin SA. New rabies vaccine halts disease — without severe reactions. Mod Med. 1977;45(20):45-8.
17. Plotkin SA, Wiktor TJ, Koprowski H, et al. Immunization schedules for the new human diploid cell vaccine against rabies. Am J Epidemiol. 1976;103(1):75-80.
18. Hafkin B, Hattwick MA, Smith JS, et al. A comparison of a WI-38 vaccine and duck embryo vaccine for preexposure rabies prophylaxis. Am J Epidemiol. 1978;107(5):439-43.
19. Kuwert EK, Marcus I, Höher PG. Neutralizing and complement-fixing antibody responses in pre- and post-exposure vaccinees to a rabies vaccine produced in human diploid cells. J Biol Stand. 1976;4(4):249-62.
20. Grandien M. Evaluation of tests for rabies antibody and analysis of serum responses after administration of three different types of rabies vaccines. J Clin Microbiol. 1977;5(3):263-7.
21. Kuwert EK, Marcus I, Werner J, et al. Postexpositionelle Schutzimpfung des Menschen gegen Tollwut mit einer neu-entwickelten Gewebekulturvakzine (HDCS-Impfstoff). [Post exposure use of human diploid cell culture rabies vaccine (author's transl)]. Zentralbl Bakteriol [A].1977;239(4):437-58.
22. Bahmanyar M, Fayaz A, Nour-Salehi S, et al. Successful protection of humans exposed to rabies infection: postexposure treatment with the new human diploid cell rabies vaccine and antirabies serum. JAMA. 1976;236(24):2751-4.
23. Helmick CG, Johnstone C, Sumner J, et al. A clinical study of Merieux human rabies immune globulin. J Biol Stand. 1982;10:357-67.
24. Lang J, Gravenstein S, Briggs D, et al. Evaluation of the safety and immunogenicity of a new, heat-treated human rabies immune globulin using a sham, post-exposure prophylaxis of rabies. Biologicals. 1998;26:7-15.

16 HOW SUPPLIED/STORAGE AND HANDLING

HYPERRAB is supplied in 1 mL, 3 mL and 5 mL single-dose vials of ready-to-use solution with a potency value of not less than 300 IU/mL.

HYPERRAB contains no preservative and is not made with natural rubber latex.

NDC Number | Size
13533-318-01 | 1 mL
13533-318-03 | 3 mL
13533-318-05 | 5 mL

- Store HYPERRAB at 2 to 8°C (36 to 46°F). Do not freeze.
  - HYPERRAB may be stored at room temperatures not to exceed 25ºC (77ºF) for up to 6 months.
  - Use within 6 months after removal from refrigeration at any time prior to the expiration date, after which the product must be used or discarded. Do not return to refrigeration.
- Do not use after expiration date printed on the label.
- Discard unused portion.

17 PATIENT COUNSELING INFORMATION

Discuss the risks and benefits of this product with the patient, before prescribing or administering it to the patient.

Inform the patient who is allergic to human immune globulin products that severe, potentially life-threatening allergic reactions could occur. [see Warnings and Precautions (5.1)]

Inform the patient who is deficient in IgA the potential for developing anti-IgA antibodies and severe potentially life-threatening allergic reactions. [see Warnings and Precautions (5.1)]

Inform the patient that HYPERRAB is made from human plasma and may carry a risk of transmitting infectious agents that can cause disease. While the risk that HYPERRAB can transmit an infectious agent has been reduced by screening plasma donors for prior exposure, testing donated plasma, and including manufacturing steps with the capacity to inactivate and/or remove pathogens, the patient should report any symptoms that concern them. [see Warnings and Precautions (‎5.2)]

Grifols Therapeutics LLC
Research Triangle Park, NC 27709 USA
U.S. License Number 1871
3063803

PACKAGE LABEL

Rabies
Immune
Globulin
(Human)
HyperRAB®
300 IU / 1 mL
1 mL
Solution for Infiltration
and Intramuscular Injection
300 IU/mL
FOR INFILTRATION AND
INTRAMUSCULAR INJECTION ONLY.
DO NOT GIVE INTRAVENOUSLY.
NDC 13533-318-01
GRIFOLS
The patient and physician
should discuss the risks and
benefits of this product.
One Single-Dose Vial
Discard unused portion.
For complete dosage and
administration information,
read enclosed package insert.
1 mL
If the shrink band is absent or
shows any sign of tampering,
do not use the product and
notify Grifols Therapeutics LLC
immediately.
Not returnable for credit or
exchange.
Rx only
GRIFOLS
Rabies Immune Globulin (Human)
is a sterile solution of
immunoglobulin containing
15%-18% protein stabilized with
0.16 to 0.26 M glycine.
The potency of each vial is
300 IU/mL based on the U.S.
Standard Rabies Immune Globulin.
1 mL
Suitable for use with Rabies Vaccine.
Not made with natural rubber latex.
No preservative
Grifols Therapeutics LLC
Research Triangle Park,
NC 27709 USA
U.S. License No. 1871
GRIFOLS
Store at 2–8ºC (36–46ºF)
AND, optionally, store at room
temperatures not to exceed
25ºC (77ºF) for up to 6 months
at any time prior to the
expiration date, after which
the product must be used or
discarded. Do not return to
refrigeration.
1 mL
Do not use after the expiration
date.
Do not freeze.
Date removed from
refrigeration:
GRIFOLS
Carton: 3060190
NDC 13533-318-01
GTIN 00313533318017
LOT XXXXXXXXXX
EXP DDMMMYYYY
SN XXXXXXXXXXXXXXXX
HyperRAB® 300 IU / 1 mL

NDC 13533-318-10
Rabies Immune
Globulin (Human)
HyperRAB®
300 IU / 1 mL
The patient and physician should
discuss the risks and benefits of
this product.
Grifols Therapeutics LLC
RTP, NC 27709 USA
U.S. License No. 1871
300 IU / 1 mL
One Single-Dose Vial
Do not give intravenously.
Dosage: 20 IU/kg in
conjunction with Rabies
Vaccine.
Discard unused portion.
See directions before using.
Rx only
3060187
Lot / Exp.

Rabies
Immune
Globulin
(Human)
HyperRAB®
900 IU / 3 mL
3 mL
Solution for Infiltration
and Intramuscular Injection
300 IU/mL
FOR INFILTRATION AND
INTRAMUSCULAR INJECTION ONLY.
DO NOT GIVE INTRAVENOUSLY.
NDC 13533-318-03
GRIFOLS
The patient and physician
should discuss the risks
and benefits of this product.
One Single-Dose Vial
Discard unused portion.
For complete dosage and
administration information,
read enclosed package insert.
3 mL
If the shrink band is absent or
shows any sign of tampering,
do not use the product and
notify Grifols Therapeutics LLC
immediately.
Not returnable for credit or
exchange.
Rx only
GRIFOLS
Rabies Immune Globulin (Human)
is a sterile solution of
immunoglobulin containing
15%-18% protein stabilized with
0.16 to 0.26 M glycine.
The potency of each vial is
300 IU/mL based on the U.S.
Standard Rabies Immune Globulin.
3 mL
Suitable for use with Rabies Vaccine.
Not made with natural rubber latex.
No preservative
Grifols Therapeutics LLC
Research Triangle Park,
NC 27709 USA
U.S. License No. 1871
GRIFOLS
Store at 2–8ºC (36–46ºF)
AND, optionally, store at room
temperatures not to exceed
25ºC (77ºF) for up to 6 months
at any time prior to the
expiration date, after which
the product must be used or
discarded. Do not return to
refrigeration.
3 mL
Do not use after the expiration
date.
Do not freeze.
Date removed from
refrigeration:
GRIFOLS
Carton: 3060191
NDC 13533-318-03
GTIN 00313533318031
LOT XXXXXXXXXXX
EXP DDMMMYYYY
SN XXXXXXXXXXXXXXXX
HyperRAB® 900 IU / 3 mL

NDC 13533-318-30
Rabies Immune
Globulin (Human)
HyperRAB®
900 IU / 3 mL (300 IU/mL)
The patient and physician should
discuss the risks and benefits of
this product.
Grifols Therapeutics LLC
RTP, NC 27709 USA
U.S. License No. 1871
900 IU / 3 mL
One Single-Dose Vial
Do not give intravenously.
Dosage: 20 IU/kg in
conjunction with Rabies
Vaccine.
Discard unused portion.
See directions before using.
Rx only
3060188
Lot / Exp.

Rabies
Immune
Globulin
(Human)
HyperRAB®
1500 IU / 5 mL
5 mL
Solution for Infiltration
and Intramuscular Injection
300 IU/mL
FOR INFILTRATION AND
INTRAMUSCULAR INJECTION ONLY.
DO NOT GIVE INTRAVENOUSLY.
NDC 13533-318-05
GRIFOLS
The patient and physician
should discuss the risks
and benefits of this product.
One Single-Dose Vial
Discard unused portion.
For complete dosage and
administration information,
read enclosed package insert.
5 mL
If the shrink band is absent or
shows any sign of tampering,
do not use the product and
notify Grifols Therapeutics LLC
immediately.
Not returnable for credit or
exchange.
Rx only
GRIFOLS
Rabies Immune Globulin (Human)
is a sterile solution of
immunoglobulin containing
15%-18% protein stabilized with
0.16 to 0.26 M glycine.
The potency of each vial is
300 IU/mL based on the U.S.
Standard Rabies Immune Globulin.
5 mL
Suitable for use with Rabies Vaccine.
Not made with natural rubber latex.
No preservative
Grifols Therapeutics LLC
Research Triangle Park,
NC 27709 USA
U.S. License No. 1871
GRIFOLS
Store at 2–8ºC (36–46ºF)
AND, optionally, store at room
temperatures not to exceed
25ºC (77ºF) for up to 6 months
at any time prior to the
expiration date, after which
the product must be used or
discarded. Do not return to
refrigeration.
5 mL
Do not use after the expiration
date.
Do not freeze.
Date removed from
refrigeration:
GRIFOLS
Carton: 3060192
NDC 13533-318-05
GTIN 00313533318055
LOT XXXXXXXXXXX
EXP DDMMMYYYY
SN XXXXXXXXXXXXXXXX
HyperRAB® 1500 IU / 5 mL

NDC 13533-318-50
Rabies Immune
Globulin (Human)
HyperRAB®
1500 IU / 5 mL (300 IU/mL)
The patient and physician should
discuss the risks and benefits of
this product.
Grifols Therapeutics LLC
RTP, NC 27709 USA
U.S. License No. 1871
1500 IU / 5 mL
One Single-Dose Vial
Do not give intravenously.
Dosage: 20 IU/kg in
conjunction with Rabies
Vaccine.
Discard unused portion.
See directions before using.
Rx only
3060189
Lot / Exp.